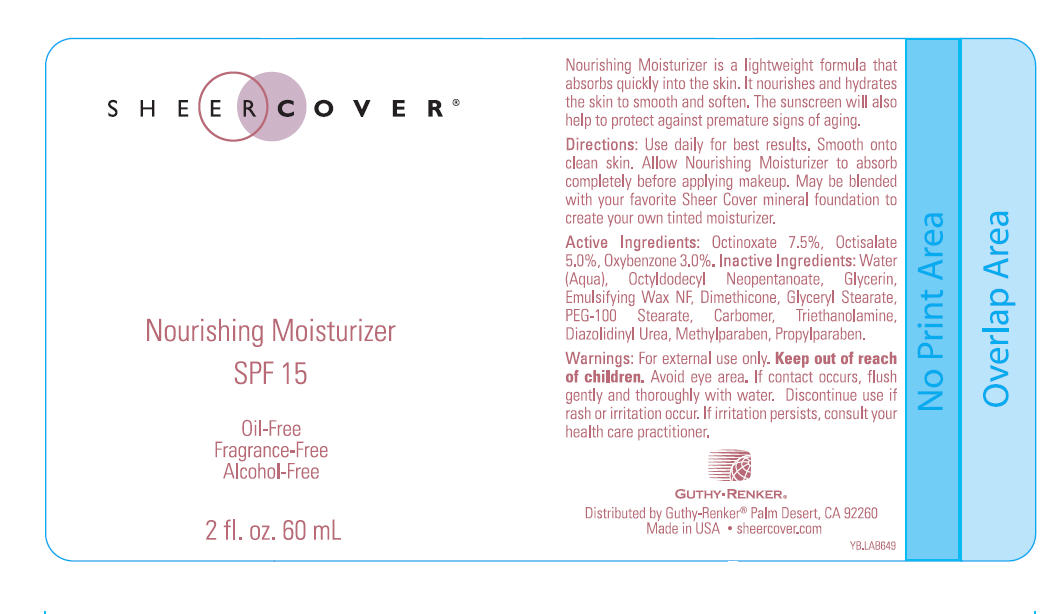 DRUG LABEL: Sheer Cover Nourishing Moisturizer
NDC: 70605-024 | Form: LOTION
Manufacturer: Guthy-Renker LLC
Category: otc | Type: HUMAN OTC DRUG LABEL
Date: 20220126

ACTIVE INGREDIENTS: OCTINOXATE 7.5 mg/100 mL; OCTISALATE 5 mg/100 mL; OXYBENZONE 3 mg/100 mL
INACTIVE INGREDIENTS: WATER; GLYCERIN; DIMETHICONE; GLYCERYL MONOSTEARATE; PEG-100 STEARATE; CARBOMER HOMOPOLYMER TYPE A (ALLYL PENTAERYTHRITOL CROSSLINKED); TROLAMINE; DIAZOLIDINYL UREA; METHYLPARABEN; PROPYLPARABEN

Sheer Cover Nourishing Moisturizer SPF 15

Drug Facts

Active Ingredients

Octinoxate 7.5%, Octisalate 5.0%, Oxybenzone 3.0%

Purpose

Sunscreen

Directions

Use daily for best results. Smooth onto clean skin. Allow Nourishing Moisturizer to absorb completely before applying makeup. May be blended with your favorite Sheer Cover mineral foundation to create your own tinted moisturizer.

Warnings

For external use only.

Keep out of reach of children.

WHEN USING

Avoid eye area. If contact occurs, flush gently and thoroughly with water.

STOP USE

Discontinue use if rash or irritation occur. If irritation persists, consult your health care practitioner.

Inactive Ingredients

Water (Aqua), Octyldodecyl Neopentanoate, Glycerin, Emulsifying Wax NF, Dimethicone , Glyceryl Stearate, PEG-100 Stearate, Carbomer, Triethanolamine, Diazolidinyl Urea, Methylparaben, Propylparaben.

PRINCIPAL DISPLAY PANEL - 60 mL Bottle Label

SHEER COVER®

Nourishing Moisturizer
SPF 15

Oil-Free
Fragrance-Free
Alcohol-Free

2 fl. oz. 60 mL